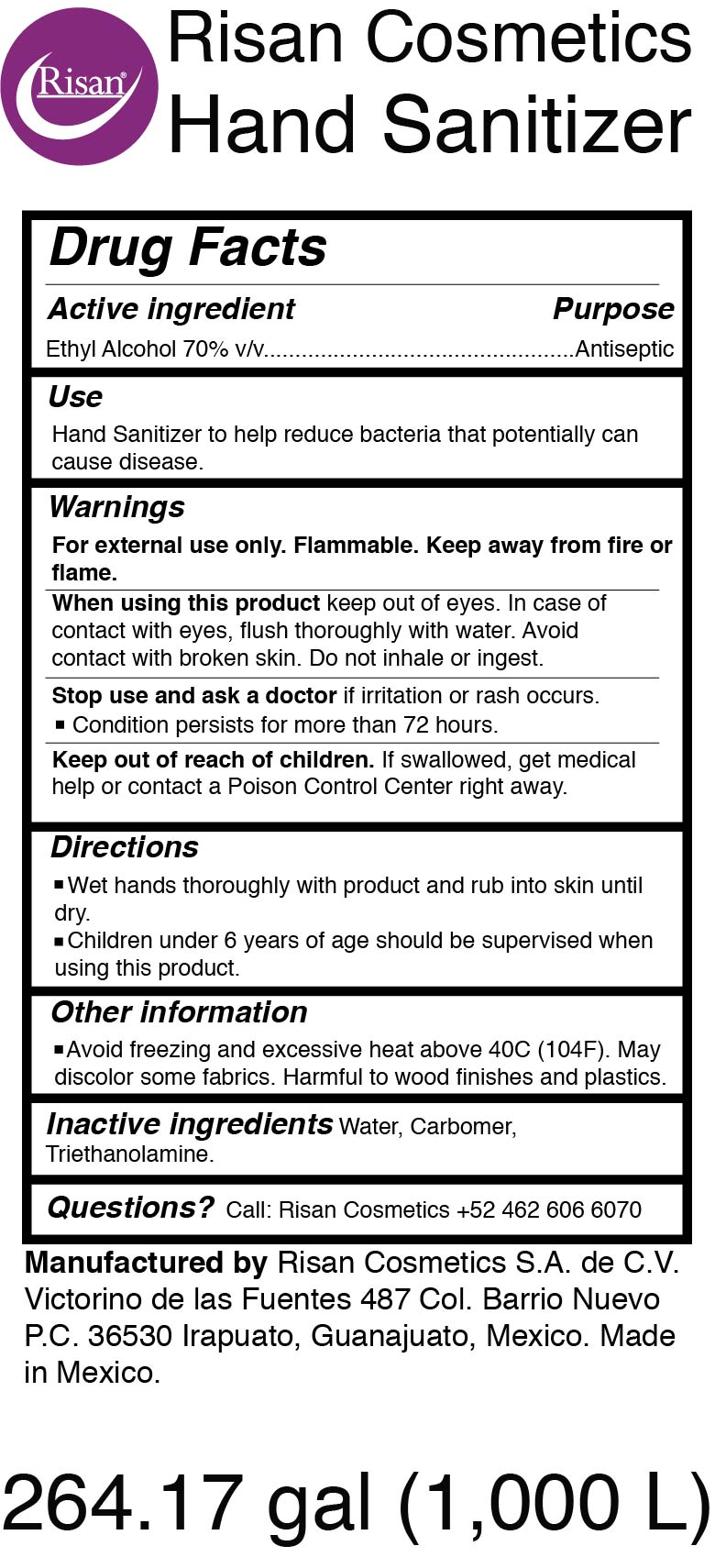 DRUG LABEL: Hand Sanitizer
NDC: 75668-200 | Form: GEL
Manufacturer: Risan Cosmetics S.A. de C.V.
Category: otc | Type: HUMAN OTC DRUG LABEL
Date: 20200511

ACTIVE INGREDIENTS: ALCOHOL 700 L/1000 L
INACTIVE INGREDIENTS: CARBOMER 940 6 L/1000 L; TROLAMINE 10 L/1000 L; WATER 284 L/1000 L

ACTIVE INGREDIENT

Ethyl Alcohol 70% v/v

PURPOSE

Antiseptic

INDICATIONS AND USAGE

Hand Sanitizer to help reduce bacteria that potentially can cause disease.

WARNINGS

For external use only. Flammable. Keep away from fire or flame.

WHEN USING

keep out of eyes. In case of contact with eyes, flush thoroughly with water. Avoid

contact with broken skin. Do not inhale or ingest.

STOP USE

and ask a doctor if irritation or rash occurs.

- Condition persists for more than 72 hours.

KEEP OUT OF REACH OF CHILDREN

If swallowed, get medical help or contact a Poison Control Center right away.

DOSAGE AND ADMINISTRATION

- Wet hands thoroughly with product and rub into skin until dry.
- Children under 6 years of age should be supervised when using this product.

OTHER SAFETY INFORMATION

Avoid freezing and excessive heat above 40C (104F). May discolor some fabrics. Harmful to wood finishes and plastics.

INACTIVE INGREDIENT

Water, Carbomer, Triethanolamine.

QUESTIONS

Call: Risan Cosmetics +52 462 606 6070

Manufactured by Risan Cosmetics S.A. de C.V. Victorino de las Fuentes 487 Col. Barrio Nuevo P.C. 36530 Irapuato, Guanajuato, Mexico. Made in Mexico.